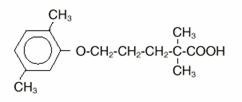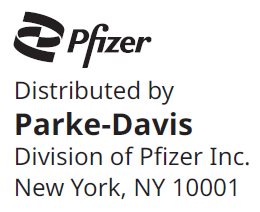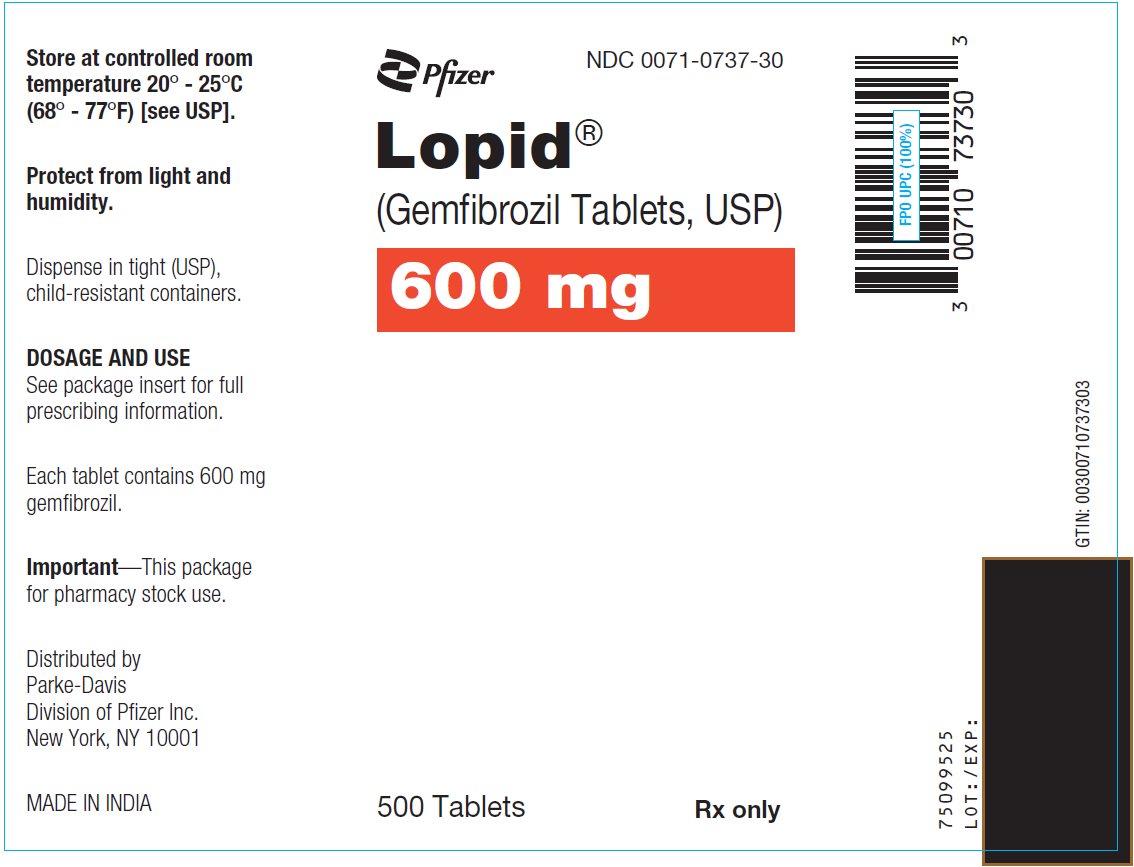 DRUG LABEL: Lopid
NDC: 0071-0737 | Form: TABLET, FILM COATED
Manufacturer: Parke-Davis Div of Pfizer Inc
Category: prescription | Type: HUMAN PRESCRIPTION DRUG LABEL
Date: 20240716

ACTIVE INGREDIENTS: GEMFIBROZIL 600 mg/1 1
INACTIVE INGREDIENTS: CALCIUM STEARATE; CANDELILLA WAX; MICROCRYSTALLINE CELLULOSE; HYDROXYPROPYL CELLULOSE (1600000 WAMW); HYPROMELLOSE, UNSPECIFIED; METHYLPARABEN; POLYETHYLENE GLYCOL, UNSPECIFIED; POLYSORBATE 80; PROPYLPARABEN; SILICON DIOXIDE

LOPID®
(Gemfibrozil Tablets, USP)

DESCRIPTION

LOPID® (gemfibrozil tablets, USP) is a lipid regulating agent. It is available as tablets for oral administration. Each tablet contains 600 mg gemfibrozil. Each tablet also contains calcium stearate, NF; candelilla wax, FCC; microcrystalline cellulose, NF; hydroxypropyl cellulose, NF; hypromellose, USP; methylparaben, NF; Opaspray white; polyethylene glycol, NF; polysorbate 80, NF; propylparaben, NF; colloidal silicon dioxide, NF; pregelatinized starch, NF. The chemical name is 5-(2,5-dimethylphenoxy)-2,2-dimethylpentanoic acid, with the following structural formula:

The empirical formula is C15H22O3 and the molecular weight is 250.35; the solubility in water and acid is 0.0019% and in dilute base it is greater than 1%. The melting point is 58° –61°C. Gemfibrozil is a white solid which is stable under ordinary conditions.

CLINICAL PHARMACOLOGY

LOPID is a lipid regulating agent which decreases serum triglycerides and very low density lipoprotein (VLDL) cholesterol, and increases high density lipoprotein (HDL) cholesterol. While modest decreases in total and low density lipoprotein (LDL) cholesterol may be observed with LOPID therapy, treatment of patients with elevated triglycerides due to Type IV hyperlipoproteinemia often results in a rise in LDL-cholesterol. LDL-cholesterol levels in Type IIb patients with elevations of both serum LDL-cholesterol and triglycerides are, in general, minimally affected by LOPID treatment; however, LOPID usually raises HDL-cholesterol significantly in this group. LOPID increases levels of high density lipoprotein (HDL) subfractions HDL2 and HDL3, as well as apolipoproteins AI and AII. Epidemiological studies have shown that both low HDL-cholesterol and high LDL-cholesterol are independent risk factors for coronary heart disease.

In the primary prevention component of the Helsinki Heart Study, in which 4081 male patients between the ages of 40 and 55 were studied in a randomized, double-blind, placebo-controlled fashion, LOPID therapy was associated with significant reductions in total plasma triglycerides and a significant increase in high density lipoprotein cholesterol. Moderate reductions in total plasma cholesterol and low density lipoprotein cholesterol were observed for the LOPID treatment group as a whole, but the lipid response was heterogeneous, especially among different Fredrickson types. The study involved subjects with serum non-HDL-cholesterol of over 200 mg/dL and no previous history of coronary heart disease. Over the five-year study period, the LOPID group experienced a 1.4% absolute (34% relative) reduction in the rate of serious coronary events (sudden cardiac deaths plus fatal and nonfatal myocardial infarctions) compared to placebo, p=0.04 (see Table I). There was a 37% relative reduction in the rate of nonfatal myocardial infarction compared to placebo, equivalent to a treatment-related difference of 13.1 events per thousand persons. Deaths from any cause during the double-blind portion of the study totaled 44 (2.2%) in the LOPID randomization group and 43 (2.1%) in the placebo group.

Table I Reduction in CHD Rates (events per 1000 patients) by Baseline Lipids [lipid values in mg/dL at baseline] in the Helsinki Heart Study, Years 0–5 [P = placebo group; L= LOPID group]
 | All Patients |  |  | LDL-C>175; HDL-C>46.4 |  |  | LDL-C>175; TG>177 |  |  | LDL-C>175; TG>200; HDL-C<35
 | P | L | Dif [difference in rates between placebo and LOPID groups] | P | L | Dif | P | L | Dif | P | L | Dif
Incidence of Events [fatal and nonfatal myocardial infarctions plus sudden cardiac deaths (events per 1000 patients over 5 years)] | 41 | 27 | 14 | 32 | 29 | 3 | 71 | 44 | 27 | 149 | 64 | 85

Among Fredrickson types, during the 5-year double-blind portion of the primary prevention component of the Helsinki Heart Study, the greatest reduction in the incidence of serious coronary events occurred in Type IIb patients who had elevations of both LDL-cholesterol and total plasma triglycerides. This subgroup of Type IIb gemfibrozil group patients had a lower mean HDL-cholesterol level at baseline than the Type IIa subgroup that had elevations of LDL-cholesterol and normal plasma triglycerides. The mean increase in HDL-cholesterol among the Type IIb patients in this study was 12.6% compared to placebo. The mean change in LDL-cholesterol among Type IIb patients was –4.1% with LOPID compared to a rise of 3.9% in the placebo subgroup. The Type IIb subjects in the Helsinki Heart Study had 26 fewer coronary events per thousand persons over five years in the gemfibrozil group compared to placebo. The difference in coronary events was substantially greater between LOPID and placebo for that subgroup of patients with the triad of LDL-cholesterol >175 mg/dL (>4.5 mmol), triglycerides >200 mg/dL (>2.2 mmol), and HDL-cholesterol <35 mg/dL (<0.90 mmol) (see Table I).

Further information is available from a 3.5 year (8.5 year cumulative) follow-up of all subjects who had participated in the Helsinki Heart Study. At the completion of the Helsinki Heart Study, subjects could choose to start, stop, or continue to receive LOPID; without knowledge of their own lipid values or double-blind treatment, 60% of patients originally randomized to placebo began therapy with LOPID and 60% of patients originally randomized to LOPID continued medication. After approximately 6.5 years following randomization, all patients were informed of their original treatment group and lipid values during the five years of the double-blind treatment. After further elective changes in LOPID treatment status, 61% of patients in the group originally randomized to LOPID were taking drug; in the group originally randomized to placebo, 65% were taking LOPID. The event rate per 1000 occurring during the open-label follow-up period is detailed in Table II.

Table II Cardiac Events and All-Cause Mortality (events per 1000 patients) Occurring During the 3.5 Year Open-Label Follow-up to the Helsinki Heart Study [The six open-label groups are designated first by the original randomization (P = placebo, L = LOPID) and then by the drug taken in the follow-up period (N = Attend clinic but took no drug, L = LOPID, Drop = No attendance at clinic during open-label).]
Group: | PDrop | PN | PL | LDrop | LN | LL
 | N=215 | N=494 | N=1283 | N=221 | N=574 | N=1207
Cardiac
Events | 38.8 | 22.9 | 22.5 | 37.2 | 28.3 | 25.4
All-Cause
Mortality | 41.9 | 22.3 | 15.6 | 72.3 | 19.2 | 24.9

Cumulative mortality through 8.5 years showed a 20% relative excess of deaths in the group originally randomized to LOPID versus the originally randomized placebo group and a 20% relative decrease in cardiac events in the group originally randomized to LOPID versus the originally randomized placebo group (see Table III). This analysis of the originally randomized "intent-to-treat'' population neglects the possible complicating effects of treatment switching during the open-label phase. Adjustment of hazard ratios, taking into account open-label treatment status from years 6.5 to 8.5, could change the reported hazard ratios for mortality toward unity.

Table III Cardiac Events, Cardiac Deaths, Non-Cardiac Deaths, and All-Cause Mortality in the Helsinki Heart Study, Years 0–8.5 [Intention-to-Treat Analysis of originally randomized patients neglecting the open-label treatment switches and exposure to study conditions.]
Event | LOPID | Placebo | LOPID:Placebo
 | at Study | at Study | Hazard | Cl Hazard
 | Start | Start | Ratio [Hazard ratio for risk event in the group originally randomized to LOPID compared to the group originally randomized to placebo neglecting open-label treatment switch and exposure to study conditions.] | Ratio [95% confidence intervals of LOPID:placebo group hazard ratio]
Cardiac
Events [Fatal and non-fatal myocardial infarctions plus sudden cardiac deaths over the 8.5 year period.] | 110 | 131 | 0.80 | 0.62–1.03
Cardiac
Deaths | 36 | 38 | 0.98 | 0.63–1.54
Non-Cardiac
Deaths | 65 | 45 | 1.40 | 0.95–2.05
All-Cause
Mortality | 101 | 83 | 1.20 | 0.90–1.61

It is not clear to what extent the findings of the primary prevention component of the Helsinki Heart Study can be extrapolated to other segments of the dyslipidemic population not studied (such as women, younger or older males, or those with lipid abnormalities limited solely to HDL-cholesterol) or to other lipid-altering drugs.

The secondary prevention component of the Helsinki Heart Study was conducted over five years in parallel and at the same centers in Finland in 628 middle-aged males excluded from the primary prevention component of the Helsinki Heart Study because of a history of angina, myocardial infarction, or unexplained ECG changes. The primary efficacy endpoint of the study was cardiac events (the sum of fatal and non-fatal myocardial infarctions and sudden cardiac deaths). The hazard ratio (LOPID:placebo) for cardiac events was 1.47 (95% confidence limits 0.88–2.48, p=0.14). Of the 35 patients in the LOPID group who experienced cardiac events, 12 patients suffered events after discontinuation from the study. Of the 24 patients in the placebo group with cardiac events, 4 patients suffered events after discontinuation from the study. There were 17 cardiac deaths in the LOPID group and 8 in the placebo group (hazard ratio 2.18; 95% confidence limits 0.94–5.05, p=0.06). Ten of these deaths in the LOPID group and 3 in the placebo group occurred after discontinuation from therapy. In this study of patients with known or suspected coronary heart disease, no benefit from LOPID treatment was observed in reducing cardiac events or cardiac deaths. Thus, LOPID has shown benefit only in selected dyslipidemic patients without suspected or established coronary heart disease. Even in patients with coronary heart disease and the triad of elevated LDL-cholesterol, elevated triglycerides, plus low HDL-cholesterol, the possible effect of LOPID on coronary events has not been adequately studied.

No efficacy in the patients with established coronary heart disease was observed during the Coronary Drug Project with the chemically and pharmacologically related drug, clofibrate. The Coronary Drug Project was a 6-year randomized, double-blind study involving 1000 clofibrate, 1000 nicotinic acid, and 3000 placebo patients with known coronary heart disease. A clinically and statistically significant reduction in myocardial infarctions was seen in the concurrent nicotinic acid group compared to placebo; no reduction was seen with clofibrate.

The mechanism of action of gemfibrozil has not been definitely established. In man, LOPID has been shown to inhibit peripheral lipolysis and to decrease the hepatic extraction of free fatty acids, thus reducing hepatic triglyceride production. LOPID inhibits synthesis and increases clearance of VLDL carrier apolipoprotein B, leading to a decrease in VLDL production.

Animal studies suggest that gemfibrozil may, in addition to elevating HDL-cholesterol, reduce incorporation of long-chain fatty acids into newly formed triglycerides, accelerate turnover and removal of cholesterol from the liver, and increase excretion of cholesterol in the feces. LOPID is well absorbed from the gastrointestinal tract after oral administration. Peak plasma levels occur in 1 to 2 hours with a plasma half-life of 1.5 hours following multiple doses.

Gemfibrozil is completely absorbed after oral administration of LOPID tablets, reaching peak plasma concentrations 1 to 2 hours after dosing. Gemfibrozil pharmacokinetics are affected by the timing of meals relative to time of dosing. In one study (ref. 4), both the rate and extent of absorption of the drug were significantly increased when administered 0.5 hour before meals. Average AUC was reduced by 14–44% when LOPID was administered after meals compared to 0.5 hour before meals. In a subsequent study, rate of absorption of LOPID was maximum when administered 0.5 hour before meals with the Cmax 50–60% greater than when given either with meals or fasting. In this study, there were no significant effects on AUC of timing of dose relative to meals (see DOSAGE AND ADMINISTRATION).

LOPID mainly undergoes oxidation of a ring methyl group to successively form a hydroxymethyl and a carboxyl metabolite. Approximately seventy percent of the administered human dose is excreted in the urine, mostly as the glucuronide conjugate, with less than 2% excreted as unchanged gemfibrozil. Six percent of the dose is accounted for in the feces. Gemfibrozil is highly bound to plasma proteins and there is potential for displacement interactions with other drugs (see PRECAUTIONS).

INDICATIONS AND USAGE

LOPID (gemfibrozil tablets, USP) is indicated as adjunctive therapy to diet for:

1. Treatment of adult patients with very high elevations of serum triglyceride levels (Types IV and V hyperlipidemia) who present a risk of pancreatitis and who do not respond adequately to a determined dietary effort to control them. Patients who present such risk typically have serum triglycerides over 2000 mg/dL and have elevations of VLDL-cholesterol as well as fasting chylomicrons (Type V hyperlipidemia). Subjects who consistently have total serum or plasma triglycerides below 1000 mg/dL are unlikely to present a risk of pancreatitis. LOPID therapy may be considered for those subjects with triglyceride elevations between 1000 and 2000 mg/dL who have a history of pancreatitis or of recurrent abdominal pain typical of pancreatitis. It is recognized that some Type IV patients with triglycerides under 1000 mg/dL may, through dietary or alcoholic indiscretion, convert to a Type V pattern with massive triglyceride elevations accompanying fasting chylomicronemia, but the influence of LOPID therapy on the risk of pancreatitis in such situations has not been adequately studied. Drug therapy is not indicated for patients with Type I hyperlipoproteinemia, who have elevations of chylomicrons and plasma triglycerides, but who have normal levels of very low density lipoprotein (VLDL). Inspection of plasma refrigerated for 14 hours is helpful in distinguishing Types I, IV, and V hyperlipoproteinemia.
2. Reducing the risk of developing coronary heart disease only in Type IIb patients without history of or symptoms of existing coronary heart disease who have had an inadequate response to weight loss, dietary therapy, exercise, and other pharmacologic agents (such as bile acid sequestrants and nicotinic acid, known to reduce LDL- and raise HDL-cholesterol) and who have the following triad of lipid abnormalities: low HDL-cholesterol levels in addition to elevated LDL-cholesterol and elevated triglycerides (see WARNINGS, PRECAUTIONS, and CLINICAL PHARMACOLOGY). The National Cholesterol Education Program has defined a serum HDL-cholesterol value that is consistently below 35 mg/dL as constituting an independent risk factor for coronary heart disease. Patients with significantly elevated triglycerides should be closely observed when treated with gemfibrozil. In some patients with high triglyceride levels, treatment with gemfibrozil is associated with a significant increase in LDL-cholesterol. BECAUSE OF POTENTIAL TOXICITY SUCH AS MALIGNANCY, GALLBLADDER DISEASE, ABDOMINAL PAIN LEADING TO APPENDECTOMY AND OTHER ABDOMINAL SURGERIES, AN INCREASED INCIDENCE IN NON-CORONARY MORTALITY, AND THE 44% RELATIVE INCREASE DURING THE TRIAL PERIOD IN AGE-ADJUSTED ALL-CAUSE MORTALITY SEEN WITH THE CHEMICALLY AND PHARMACOLOGICALLY RELATED DRUG, CLOFIBRATE, THE POTENTIAL BENEFIT OF GEMFIBROZIL IN TREATING TYPE IIA PATIENTS WITH ELEVATIONS OF LDL-CHOLESTEROL ONLY IS NOT LIKELY TO OUTWEIGH THE RISKS. LOPID IS ALSO NOT INDICATED FOR THE TREATMENT OF PATIENTS WITH LOW HDL-CHOLESTEROL AS THEIR ONLY LIPID ABNORMALITY.

In a subgroup analysis of patients in the Helsinki Heart Study with above-median HDL-cholesterol values at baseline (greater than 46.4 mg/dL), the incidence of serious coronary events was similar for gemfibrozil and placebo subgroups (see Table I).

The initial treatment for dyslipidemia is dietary therapy specific for the type of lipoprotein abnormality. Excess body weight and excess alcohol intake may be important factors in hypertriglyceridemia and should be managed prior to any drug therapy. Physical exercise can be an important ancillary measure, and has been associated with rises in HDL-cholesterol. Diseases contributory to hyperlipidemia such as hypothyroidism or diabetes mellitus should be looked for and adequately treated. Estrogen therapy is sometimes associated with massive rises in plasma triglycerides, especially in subjects with familial hypertriglyceridemia. In such cases, discontinuation of estrogen therapy may obviate the need for specific drug therapy of hypertriglyceridemia. The use of drugs should be considered only when reasonable attempts have been made to obtain satisfactory results with nondrug methods. If the decision is made to use drugs, the patient should be instructed that this does not reduce the importance of adhering to diet.

CONTRAINDICATIONS

1. Hepatic or severe renal dysfunction, including primary biliary cirrhosis.
2. Preexisting gallbladder disease (see WARNINGS).
3. Hypersensitivity to gemfibrozil.
4. Combination therapy of gemfibrozil with simvastatin (see WARNINGS and PRECAUTIONS).
5. Combination therapy of gemfibrozil with repaglinide (see PRECAUTIONS).
6. Combination therapy of gemfibrozil with dasabuvir (see PRECAUTIONS).
7. Combination therapy of gemfibrozil with selexipag (see PRECAUTIONS).

WARNINGS

1. Because of chemical, pharmacological, and clinical similarities between gemfibrozil and clofibrate, the adverse findings with clofibrate in two large clinical studies may also apply to gemfibrozil. In the first of those studies, the Coronary Drug Project, 1000 subjects with previous myocardial infarction were treated for five years with clofibrate. There was no difference in mortality between the clofibrate-treated subjects and 3000 placebo-treated subjects, but twice as many clofibrate-treated subjects developed cholelithiasis and cholecystitis requiring surgery. In the other study, conducted by the World Health Organization (WHO), 5000 subjects without known coronary heart disease were treated with clofibrate for five years and followed one year beyond. There was a statistically significant (44%) higher age-adjusted total mortality in the clofibrate-treated group than in a comparable placebo-treated control group during the trial period. The excess mortality was due to a 33% increase in non-cardiovascular causes, including malignancy, post-cholecystectomy complications, and pancreatitis. The higher risk of clofibrate-treated subjects for gallbladder disease was confirmed.

Because of the more limited size of the Helsinki Heart Study, the observed difference in mortality from any cause between the LOPID and placebo groups is not statistically significantly different from the 29% excess mortality reported in the clofibrate group in the separate WHO study at the nine year follow-up (see CLINICAL PHARMACOLOGY). Noncoronary heart disease related mortality showed an excess in the group originally randomized to LOPID primarily due to cancer deaths observed during the open-label extension.

During the five year primary prevention component of the Helsinki Heart Study, mortality from any cause was 44 (2.2%) in the LOPID group and 43 (2.1%) in the placebo group; including the 3.5 year follow-up period since the trial was completed, cumulative mortality from any cause was 101 (4.9%) in the LOPID group and 83 (4.1%) in the group originally randomized to placebo (hazard ratio 1:20 in favor of placebo). Because of the more limited size of the Helsinki Heart Study, the observed difference in mortality from any cause between the LOPID and placebo groups at Year-5 or at Year-8.5 is not statistically significantly different from the 29% excess mortality reported in the clofibrate group in the separate WHO study at the nine year follow-up. Noncoronary heart disease related mortality showed an excess in the group originally randomized to LOPID at the 8.5 year follow-up (65 LOPID versus 45 placebo noncoronary deaths).

The incidence of cancer (excluding basal cell carcinoma) discovered during the trial and in the 3.5 years after the trial was completed was 51 (2.5%) in both originally randomized groups. In addition, there were 16 basal cell carcinomas in the group originally randomized to LOPID and 9 in the group originally randomized to placebo (p=0.22). There were 30 (1.5%) deaths attributed to cancer in the group originally randomized to LOPID and 18 (0.9%) in the group originally randomized to placebo (p=0.11). Adverse outcomes, including coronary events, were higher in gemfibrozil patients in a corresponding study in men with a history of known or suspected coronary heart disease in the secondary prevention component of the Helsinki Heart Study (see CLINICAL PHARMACOLOGY).

A comparative carcinogenicity study was also done in rats comparing three drugs in this class: fenofibrate (10 and 60 mg/kg; 0.3 and 1.6 times the human dose, respectively), clofibrate (400 mg/kg; 1.6 times the human dose), and gemfibrozil (250 mg/kg; 1.7 times the human dose). Pancreatic acinar adenomas were increased in males and females on fenofibrate; hepatocellular carcinoma and pancreatic acinar adenomas were increased in males and hepatic neoplastic nodules in females treated with clofibrate; hepatic neoplastic nodules were increased in males and females treated with clofibrate; hepatic neoplastic nodules were increased in males and females treated with gemfibrozil while testicular interstitial cell (Leydig cell) tumors were increased in males on all three drugs.

2. A gallstone prevalence substudy of 450 Helsinki Heart Study participants showed a trend toward a greater prevalence of gallstones during the study within the LOPID treatment group (7.5% versus 4.9% for the placebo group, a 55% excess for the gemfibrozil group). A trend toward a greater incidence of gallbladder surgery was observed for the LOPID group (17 versus 11 subjects, a 54% excess). This result did not differ statistically from the increased incidence of cholecystectomy observed in the WHO study in the group treated with clofibrate. Both clofibrate and gemfibrozil may increase cholesterol excretion into the bile, leading to cholelithiasis. If cholelithiasis is suspected, gallbladder studies are indicated. LOPID therapy should be discontinued if gallstones are found. Cases of cholelithiasis have been reported with gemfibrozil therapy.

3. Since a reduction of mortality from coronary heart disease has not been demonstrated and because liver and interstitial cell testicular tumors were increased in rats, LOPID should be administered only to those patients described in the INDICATIONS AND USAGE section. If a significant serum lipid response is not obtained, LOPID should be discontinued.

4. Concomitant Anticoagulants – Caution should be exercised when warfarin is given in conjunction with LOPID. The dosage of warfarin should be reduced to maintain the prothrombin time at the desired level to prevent bleeding complications. Frequent prothrombin determinations are advisable until it has been definitely determined that the prothrombin level has stabilized.

5. The concomitant administration of LOPID with simvastatin is contraindicated (see CONTRAINDICATIONS and PRECAUTIONS). Concomitant therapy with LOPID and an HMG-CoA reductase inhibitor is associated with an increased risk of skeletal muscle toxicity manifested as rhabdomyolysis, markedly elevated creatine kinase (CPK) levels, and myoglobinuria, leading in a high proportion of cases to acute renal failure and death. IN PATIENTS WHO HAVE HAD AN UNSATISFACTORY LIPID RESPONSE TO EITHER DRUG ALONE, THE BENEFIT OF COMBINED THERAPY WITH LOPID AND an HMG-CoA REDUCTASE INHIBITOR DOES NOT OUTWEIGH THE RISKS OF SEVERE MYOPATHY, RHABDOMYOLYSIS, AND ACUTE RENAL FAILURE (see PRECAUTIONS, Drug Interactions). The use of fibrates alone, including LOPID, may occasionally be associated with myositis. Patients receiving LOPID and complaining of muscle pain, tenderness, or weakness should have prompt medical evaluation for myositis, including serum creatine–kinase level determination. If myositis is suspected or diagnosed, LOPID therapy should be withdrawn.

6. Cataracts – Subcapsular bilateral cataracts occurred in 10%, and unilateral in 6.3%, of male rats treated with gemfibrozil at 10 times the human dose.

7. CYP2C8 substrates - Gemfibrozil, a strong inhibitor of CYP2C8, may increase exposure of CYP2C8 substrates when administered concomitantly (see PRECAUTIONS, Drug Interactions).

8. OATP1B1 substrates – Gemfibrozil is an inhibitor of organic anion-transporter polyprotein (OATP) 1B1 and may increase exposure of drugs that are substrates of OATP1B1 (e.g., atrasentan, atorvastatin, bosentan, ezetimibe, fluvastatin, glyburide, SN-38 [active metabolite of irinotecan], rosuvastatin, pitavastatin, pravastatin, rifampin, valsartan, olmesartan). Therefore, dosing reductions of drugs that are substrates of OATP1B1 may be required when gemfibrozil is used concomitantly (see PRECAUTIONS, Drug Interactions). Combination therapy of gemfibrozil with simvastatin or with repaglinide, which are OATP1B1 substrates, is contraindicated (see CONTRAINDICATIONS).

PRECAUTIONS

1. Initial Therapy

Laboratory studies should be done to ascertain that the lipid levels are consistently abnormal. Before instituting LOPID therapy, every attempt should be made to control serum lipids with appropriate diet, exercise, weight loss in obese patients, and control of any medical problems such as diabetes mellitus and hypothyroidism that are contributing to the lipid abnormalities.

2. Continued Therapy

Periodic determination of serum lipids should be obtained, and the drug withdrawn if lipid response is inadequate after three months of therapy.

3. Drug Interactions

(A) HMG-CoA Reductase Inhibitors

The concomitant administration of LOPID with simvastatin is contraindicated (see CONTRAINDICATIONS and WARNINGS). Avoid concomitant use of LOPID with rosuvastatin. If concomitant use cannot be avoided, initiate rosuvastatin at 5 mg once daily. The dose of rosuvastatin should not exceed 10 mg once daily. The risk of myopathy and rhabdomyolysis is increased with combined gemfibrozil and HMG-CoA reductase inhibitor therapy. Myopathy or rhabdomyolysis with or without acute renal failure have been reported as early as three weeks after initiation of combined therapy or after several months (see WARNINGS). There is no assurance that periodic monitoring of creatine kinase will prevent the occurrence of severe myopathy and kidney damage.

(B) Anticoagulants

CAUTION SHOULD BE EXERCISED WHEN WARFARIN IS GIVEN IN CONJUNCTION WITH LOPID. THE DOSAGE OF WARFARIN SHOULD BE REDUCED TO MAINTAIN THE PROTHROMBIN TIME AT THE DESIRED LEVEL TO PREVENT BLEEDING COMPLICATIONS. FREQUENT PROTHROMBIN DETERMINATIONS ARE ADVISABLE UNTIL IT HAS BEEN DEFINITELY DETERMINED THAT THE PROTHROMBIN LEVEL HAS STABILIZED.

(C) CYP2C8 Substrates

Gemfibrozil is a strong inhibitor of CYP2C8 and may increase exposure of drugs mainly metabolized by CYP2C8 (e.g., dabrafenib, enzalutamide, loperamide, montelukast, paclitaxel, pioglitazone, rosiglitazone). Therefore, dosing reduction of drugs that are mainly metabolized by CYP2C8 enzyme may be required when gemfibrozil is used concomitantly (see WARNINGS).

Repaglinide

In healthy volunteers, co-administration with gemfibrozil (600 mg twice daily for 3 days) resulted in an 8.1-fold (range 5.5- to 15.0- fold) higher repaglinide AUC and a 28.6-fold (range 18.5- to 80.1-fold) higher repaglinide plasma concentration 7 hours after the dose. In the same study, gemfibrozil (600 mg twice daily for 3 days) + itraconazole (200 mg in the morning and 100 mg in the evening at Day 1, then 100 mg twice daily at Day 2–3) resulted in a 19.4- (range 12.9- to 24.7-fold) higher repaglinide AUC and a 70.4-fold (range 42.9- to 119.2-fold) higher repaglinide plasma concentration 7 hours after the dose. In addition, gemfibrozil alone or gemfibrozil + itraconazole prolonged the hypoglycemic effects of repaglinide. Co-administration of gemfibrozil and repaglinide increases the risk of severe hypoglycemia and is contraindicated (see CONTRAINDICATIONS).

Dasabuvir

Co-administration of gemfibrozil with dasabuvir increased dasabuvir AUC and Cmax (ratios: 11.3 and 2.01, respectively) due to CYP2C8 inhibition. Increased dasabuvir exposure may increase the risk of QT prolongation, therefore, co-administration of gemfibrozil with dasabuvir is contraindicated (see CONTRAINDICATIONS).

Selexipag

Co-administration of gemfibrozil with selexipag doubled exposure to selexipag and increased exposure to the active metabolite by approximately 11-fold. Concomitant administration of gemfibrozil with selexipag is contraindicated (see CONTRAINDICATIONS).

Enzalutamide

In healthy volunteers given a single 160 mg dose of enzalutamide after gemfibrozil 600 mg twice daily, the AUC of enzalutamide plus active metabolite (N-desmethyl enzalutamide) was increased by 2.2 fold and corresponding Cmax was decreased by 16%. Increased enzalutamide exposure may increase the risk of seizures. If co-administration is considered necessary, the dose of enzalutamide should be reduced (see WARNINGS).

(D) OATP1B1 substrates

Gemfibrozil is an inhibitor of OATP1B1 transporter and may increase exposure of drugs that are substrates of OATP1B1 (e.g., atrasentan, atorvastatin, bosentan, ezetimibe, fluvastatin, glyburide, SN-38 [active metabolite of irinotecan], rosuvastatin, pitavastatin, pravastatin, rifampin, valsartan, olmesartan). Therefore, dosing reductions of drugs that are substrates of OATP1B1 may be required when gemfibrozil is used concomitantly (see WARNINGS). Combination therapy of gemfibrozil with simvastatin or with repaglinide, which are OATP1B1 substrates, is contraindicated (see CONTRAINDICATIONS).

(E) In vitro studies of CYP enzymes, UGTA enzymes and OATP1B1 transporter

In vitro studies have shown that gemfibrozil is an inhibitor of CYP1A2, CYP2C8, CYP2C9, CYP2C19, OATP1B1, and UDP-glucuronosyltransferase (UGT) 1A1 and 1A3 (see WARNINGS).

(F) Bile Acid-Binding Resins

Gemfibrozil AUC was reduced by 30% when gemfibrozil was given (600 mg) simultaneously with resin-granule drugs such as colestipol (5 g). Administration of the drugs two hours or more apart is recommended because gemfibrozil exposure was not significantly affected when it was administered two hours apart from colestipol.

(G) Colchicine

Myopathy, including rhabdomyolysis, has been reported with chronic administration of colchicine at therapeutic doses. Concomitant use of LOPID may potentiate the development of myopathy. Patients with renal dysfunction and elderly patients are at increased risk. Caution should be exercised when prescribing LOPID with colchicine, especially in elderly patients or patients with renal dysfunction.

4. Carcinogenesis, Mutagenesis, Impairment of Fertility

Long-term studies have been conducted in rats at 0.2 and 1.3 times the human exposure (based on AUC). The incidence of benign liver nodules and liver carcinomas was significantly increased in high dose male rats. The incidence of liver carcinomas increased also in low dose males, but this increase was not statistically significant (p=0.1). Male rats had a dose-related and statistically significant increase of benign Leydig cell tumors. The higher dose female rats had a significant increase in the combined incidence of benign and malignant liver neoplasms.

Long-term studies have been conducted in mice at 0.1 and 0.7 times the human exposure (based on AUC). There were no statistically significant differences from controls in the incidence of liver tumors, but the doses tested were lower than those shown to be carcinogenic with other fibrates.

Electron microscopy studies have demonstrated a florid hepatic peroxisome proliferation following LOPID administration to the male rat. An adequate study to test for peroxisome proliferation has not been done in humans but changes in peroxisome morphology have been observed. Peroxisome proliferation has been shown to occur in humans with either of two other drugs of the fibrate class when liver biopsies were compared before and after treatment in the same individual.

Administration of approximately 2 times the human dose (based on surface area) to male rats for 10 weeks resulted in a dose-related decrease of fertility. Subsequent studies demonstrated that this effect was reversed after a drug-free period of about eight weeks, and it was not transmitted to the offspring.

5. Pregnancy

LOPID has been shown to produce adverse effects in rats and rabbits at doses between 0.5 and 3 times the human dose (based on surface area). There are no adequate and well-controlled studies in pregnant women. LOPID should be used during pregnancy only if the potential benefit justifies the potential risk to the fetus.

Administration of LOPID to female rats at 2 times the human dose (based on surface area) before and throughout gestation caused a dose-related decrease in conception rate, an increase in stillborns, and a slight reduction in pup weight during lactation. There were also dose-related increased skeletal variations. Anophthalmia occurred, but rarely.

Administration of 0.6 and 2 times the human dose (based on surface area) of LOPID to female rats from gestation day 15 through weaning caused dose-related decreases in birth weight and suppressions of pup growth during lactation.

Administration of 1 and 3 times the human dose (based on surface area) of LOPID to female rabbits during organogenesis caused a dose-related decrease in litter size and, at the high dose, an increased incidence of parietal bone variations.

6. Nursing Mothers

It is not known whether this drug is excreted in human milk. Because many drugs are excreted in human milk and because of the potential for tumorigenicity shown for LOPID in animal studies, a decision should be made whether to discontinue nursing or to discontinue the drug, taking into account the importance of the drug to the mother.

7. Hematologic Changes

Mild hemoglobin, hematocrit, and white blood cell decreases have been observed in occasional patients following initiation of LOPID therapy. However, these levels stabilize during long-term administration. Rarely, severe anemia, leukopenia, thrombocytopenia, and bone marrow hypoplasia have been reported. Therefore, periodic blood counts are recommended during the first 12 months of LOPID administration.

8. Liver Function

Abnormal liver function tests have been observed occasionally during LOPID administration, including elevations of AST, ALT, LDH, bilirubin, and alkaline phosphatase. These are usually reversible when LOPID is discontinued. Therefore, periodic liver function studies are recommended and LOPID therapy should be terminated if abnormalities persist.

9. Kidney Function

There have been reports of worsening renal insufficiency upon the addition of LOPID therapy in individuals with baseline plasma creatinine >2.0 mg/dL. In such patients, the use of alternative therapy should be considered against the risks and benefits of a lower dose of LOPID.

10. Pediatric Use

Safety and efficacy in pediatric patients have not been established.

ADVERSE REACTIONS

In the double-blind controlled phase of the primary prevention component of the Helsinki Heart Study, 2046 patients received LOPID for up to five years. In that study, the following adverse reactions were statistically more frequent in subjects in the LOPID group:

 | LOPID (N = 2046) | PLACEBO (N = 2035)
 | Frequency in percent of subjects
Gastrointestinal reactions | 34.2 | 23.8
Dyspepsia | 19.6 | 11.9
Abdominal pain | 9.8 | 5.6
Acute appendicitis | 1.2 | 0.6
(histologically confirmed in most cases where data were available)
Atrial fibrillation | 0.7 | 0.1
Adverse events reported by more than 1% of subjects, but without a significant difference between groups:
Diarrhea | 7.2 | 6.5
Fatigue | 3.8 | 3.5
Nausea/Vomiting | 2.5 | 2.1
Eczema | 1.9 | 1.2
Rash | 1.7 | 1.3
Vertigo | 1.5 | 1.3
Constipation | 1.4 | 1.3
Headache | 1.2 | 1.1

Gallbladder surgery was performed in 0.9% of LOPID and 0.5% of placebo subjects in the primary prevention component, a 64% excess, which is not statistically different from the excess of gallbladder surgery observed in the clofibrate group compared to the placebo group of the WHO study. Gallbladder surgery was also performed more frequently in the LOPID group compared to the placebo group (1.9% versus 0.3%, p=0.07) in the secondary prevention component. A statistically significant increase in appendectomy in the gemfibrozil group was seen also in the secondary prevention component (6 on gemfibrozil versus 0 on placebo, p=0.014).

Nervous system and special senses adverse reactions were more common in the LOPID group. These included hypesthesia, paresthesias, and taste perversion. Other adverse reactions that were more common among LOPID treatment group subjects but where a causal relationship was not established include cataracts, peripheral vascular disease, and intracerebral hemorrhage.

From other studies it seems probable that LOPID is causally related to the occurrence of MUSCULOSKELETAL SYMPTOMS (see WARNINGS), and to ABNORMAL LIVER FUNCTION TESTS and HEMATOLOGIC CHANGES (see PRECAUTIONS).

Reports of viral and bacterial infections (common cold, cough, urinary tract infections) were more common in gemfibrozil treated patients in other controlled clinical trials of 805 patients. Additional adverse reactions that have been reported for gemfibrozil are listed below by system. These are categorized according to whether a causal relationship to treatment with LOPID is probable or not established:

 | CAUSAL RELATIONSHIP PROBABLE | CAUSAL RELATIONSHIP NOT ESTABLISHED
General: Cardiac: |  | weight loss extrasystoles
Gastrointestinal: | cholestatic jaundice | pancreatitis hepatoma colitis
Central Nervous
System: | dizziness somnolence paresthesia peripheral neuritis decreased libido depression headache | confusion convulsions syncope
Eye: | blurred vision | retinal edema
Genitourinary: | impotence | decreased male fertility renal dysfunction
Musculoskeletal: | myopathy myasthenia myalgia painful extremities arthralgia synovitis rhabdomyolysis (see WARNINGS and Drug Interactions under PRECAUTIONS)
Clinical
Laboratory: | increased creatine phosphokinase increased bilirubin increased liver transaminases (AST, ALT) increased alkaline phosphatase | positive antinuclear antibody
Hematopoietic: | anemia leukopenia bone marrow hypoplasia eosinophilia | thrombocytopenia
Immunologic: | angioedema laryngeal edema urticaria | anaphylaxis Lupus-like syndrome vasculitis
Integumentary: | exfoliative dermatitis rash dermatitis pruritus | alopecia photosensitivity

Additional adverse reactions that have been reported include cholecystitis and cholelithiasis (see WARNINGS).

DOSAGE AND ADMINISTRATION

The recommended dose for adults is 1200 mg administered in two divided doses 30 minutes before the morning and evening meals (see CLINICAL PHARMACOLOGY).

OVERDOSAGE

There have been reported cases of overdosage with LOPID. In one case, a 7-year-old child recovered after ingesting up to 9 grams of LOPID. Symptoms reported with overdosage were abdominal cramps, abnormal liver function tests, diarrhea, increased CPK, joint and muscle pain, nausea and vomiting. Symptomatic supportive measures should be taken, should an overdose occur.

HOW SUPPLIED

LOPID (Tablet 737), white, elliptical, film-coated, scored tablets, each containing 600 mg gemfibrozil, are available as follows:

NDC 0071-0737-20: Bottles of 60

NDC 0071-0737-30: Bottles of 500

STORAGE AND HANDLING

Store at controlled room temperature 20° – 25°C (68° – 77°F) [see USP]. Protect from light and humidity.

LAB-0107-17.0

Revised August 2023

PRINCIPAL DISPLAY PANEL - 600 mg Tablet Bottle Label

Pfizer

NDC 0071-0737-30

Lopid®
(Gemfibrozil Tablets, USP)

600 mg

500 Tablets
Rx only